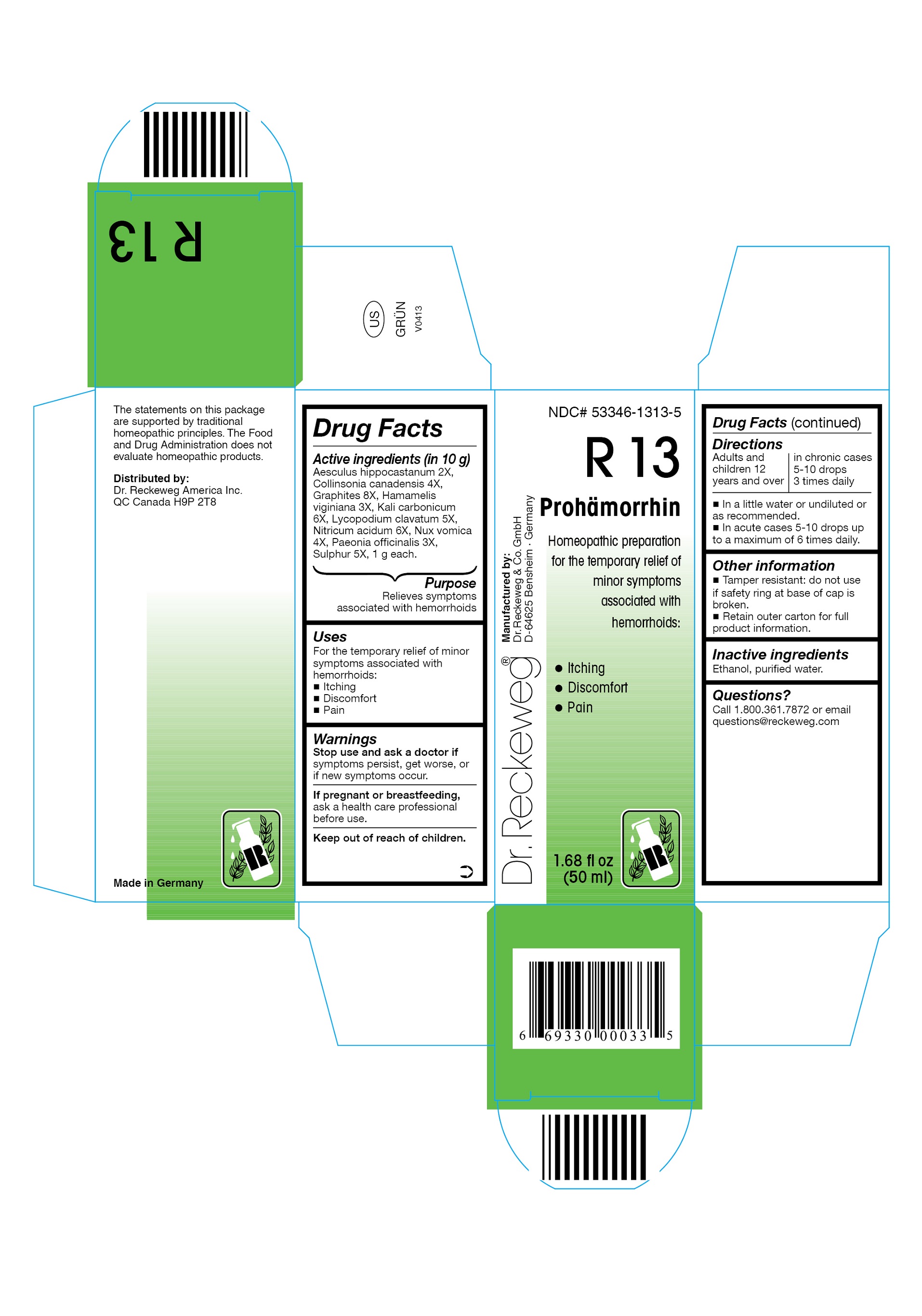 DRUG LABEL: DR. RECKEWEG R13 Prohaemorrhin
NDC: 53346-1313 | Form: LIQUID
Manufacturer: PHARMAZEUTISCHE FABRIK DR. RECKEWEG & CO
Category: homeopathic | Type: HUMAN OTC DRUG LABEL
Date: 20130403

ACTIVE INGREDIENTS: HORSE CHESTNUT 2 [hp_X]/50 mL; COLLINSONIA CANADENSIS ROOT 4 [hp_X]/50 mL; GRAPHITE 8 [hp_X]/50 mL; HAMAMELIS VIRGINIANA ROOT BARK/STEM BARK  3 [hp_X]/50 mL; POTASSIUM CARBONATE 6 [hp_X]/50 mL; LYCOPODIUM CLAVATUM SPORE 5 [hp_X]/50 mL; NITRIC ACID 6 [hp_X]/50 mL; STRYCHNOS NUX-VOMICA SEED 4 [hp_X]/50 mL; PAEONIA OFFICINALIS ROOT 3 [hp_X]/50 mL; SULFUR 5 [hp_X]/50 mL
INACTIVE INGREDIENTS: ALCOHOL; WATER

DR. RECKEWEG R13 Prohämorrhin

Active ingredients

Aesculus hippocastanum 2X, Collinsonia canadensis 4X, Graphites 8X, Hamamelis viginiana 3X, Kali carbonicum 6X, Lycopodium clavatum 5X, Nitricum acidum 6X, Nux vomica 4X, Paeonia officinalis 3X, Sulphur 5X, 1 g each in 10 g.

Purpose

Relieves symptoms associated with hemorrhoids

Uses

For the temporary relief of minor symptoms associated with hemorrhoids:

- Itching
- Discomfort
- Pain

Warnings

Stop use and ask a doctor if symptoms persist, get worse, or if new symptoms occur.

PREGNANCY OR BREAST FEEDING

If pregnant or breastfeeding, ask a health care professional before use.

Keep out of reach of children.

Directions
Adults and children ≥ 12 years: acute cases: 5-10 drops up to a maximum of 6 times daily;

in chronic cases: 5-10 drops 3 times daily in a little water or undiluted or as recommended.

Other information

- Tamper resistant: do not use if safety ring at base of cap is broken.
- Retain outer carton for full product information.

Inactive ingredients

Ethanol, purified water.

Questions?

Call 1-800-361-7872 or email questions@reckeweg.com

PACKAGE LABEL

NDC# 53346-1313-5

Dr. Reckeweg R13 Prohämorrhin

Homeopathic preparation for the temporary relief of minor symptoms associated with hemorrhoids:

- Itching
- Discomfort
- Pain

Manufactured by:

Dr. Reckeweg Co. GmbH

D-64625 Bensheim

Germany

1.68 fl oz
(50 ml)